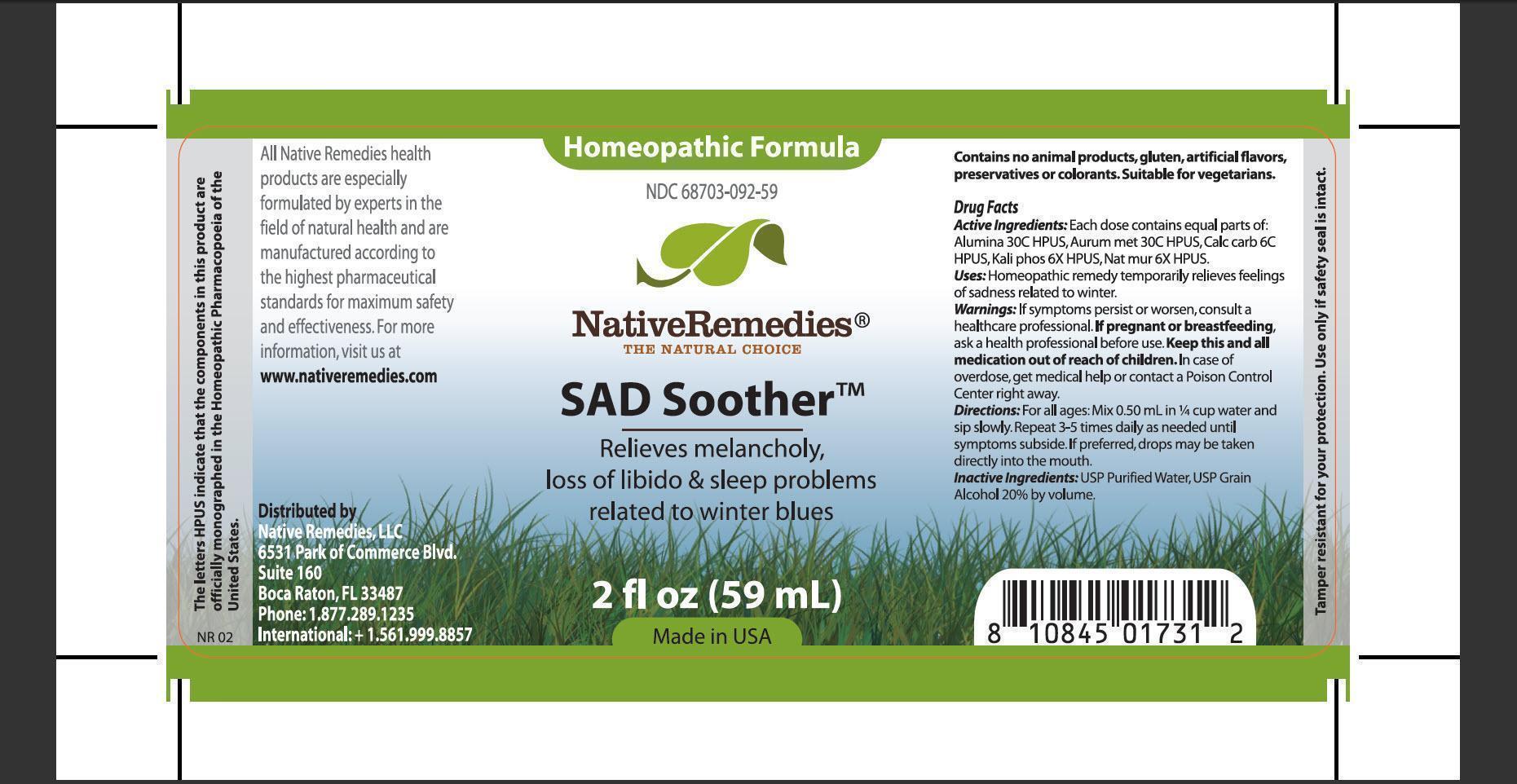 DRUG LABEL: SAD Soother
NDC: 68703-092 | Form: TINCTURE
Manufacturer: Native Remedies, LLC
Category: homeopathic | Type: HUMAN OTC DRUG LABEL
Date: 20130325

ACTIVE INGREDIENTS: ALUMINUM OXIDE 30 [hp_C]/1 mL; GOLD 30 [hp_C]/1 mL; OYSTER SHELL CALCIUM CARBONATE, CRUDE 6 [hp_C]/1 mL; POTASSIUM PHOSPHATE, DIBASIC 6 [hp_X]/1 mL; SODIUM CHLORIDE 6 [hp_X]/1 mL
INACTIVE INGREDIENTS: WATER; ALCOHOL

SAD Soother

PURPOSE

Relieves melancholy, loss of libido and sleep problems related to winter blues

ACTIVE INGREDIENT

Active Ingredients: Each dose contains equal parts of: Alumina 30C HPUS, Aurum met 30C HPUS, Calc carb 6C HPUS, Kali phos 6X HPUS, Nat mur 6X HPUS

INDICATIONS AND USAGE

Uses:Homeopathic remedy temporarily relieves feelings o sadness related to winter

WARNINGS

Warning: If symptoms persist or worsen, consult a healthcare professional

PREGNANCY OR BREAST FEEDING

If pregnant or breastfeeding, ask a health professional before use

KEEP OUT OF REACH OF CHILDREN

Keep this and all medication out of reach of children

OVERDOSAGE

In case of overdose, get medical help or contact a Poison Control Center right away

DOSAGE AND ADMINISTRATION

Directions:For all ages: Mix 0.50 mL in 1/4 cup water and sip slowly. Repeat 3-5 times daily as needed until symptoms subside. If preferred, drops may be taken directly into the mouth

INACTIVE INGREDIENT

Inactive Ingredients: USP Purified Water, USP Grain Alcohol 20% by volume

PATIENT COUNSELING INFORMATION

The letters HPUS indicate that the components in this product are officially monographed in the Homeopathic Pharmacopoeia of the Unites States

All Native Remedies health products are especially formulated by experts in the field of natural health and are manufactured according to the highest pharmaceutical standards for maximum safety and effectiveness. For more information, visit us at www.nativeremedies.com

Distributed by
Native remedies, LLC
6531 Park of Commerce Blvd.
Siute 160
Boca Raton, FL 33487
Phone: 1.877.289.1235
International: +1.561.999.8857

Contains no animal products, gluten, artificial flavors, preservatives or colorants. Suitable for vegetarians

STORAGE AND HANDLING

Tamper resistant for your protection. Use only if safety seal is intact